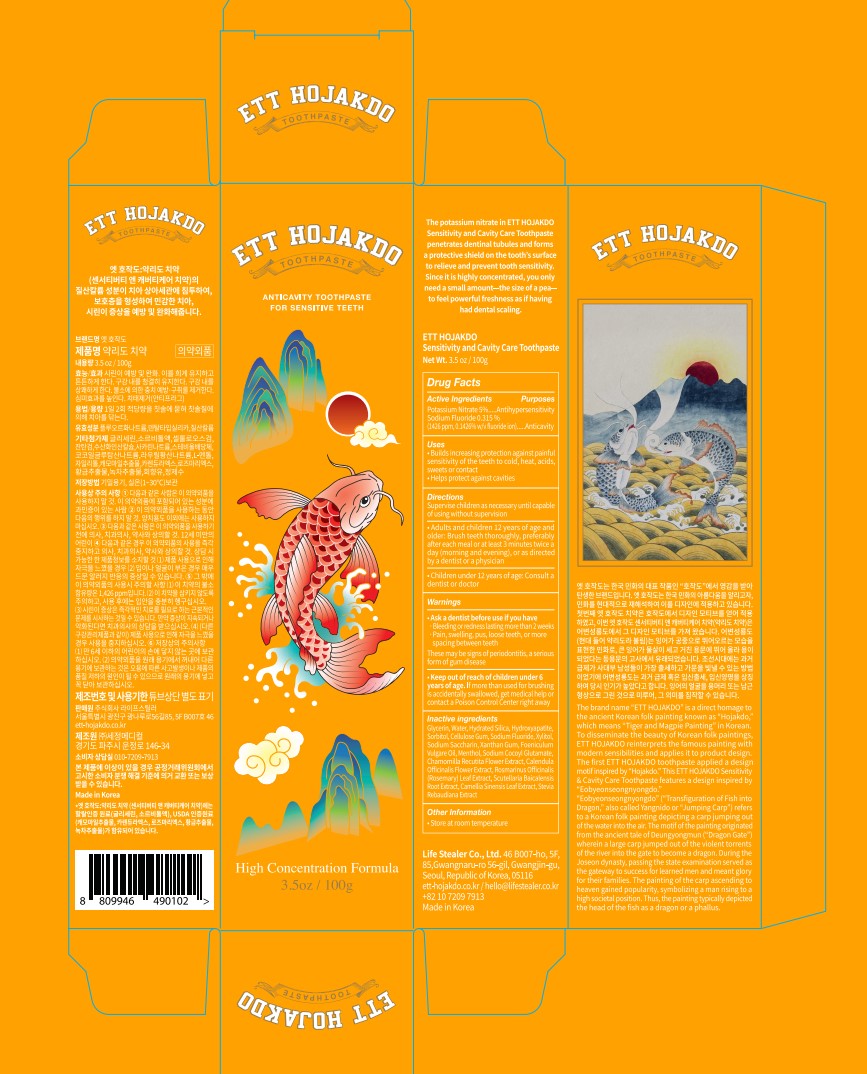 DRUG LABEL: ETT HOJAKDO Sensitivity and Cavity Care
NDC: 83672-002 | Form: PASTE, DENTIFRICE
Manufacturer: LIFE STEALER Co., Ltd.
Category: otc | Type: HUMAN OTC DRUG LABEL
Date: 20241211

ACTIVE INGREDIENTS: POTASSIUM NITRATE 5 g/100 g; SODIUM FLUORIDE 0.315 g/100 g
INACTIVE INGREDIENTS: HYDRATED SILICA; GLYCERIN; CARBOXYMETHYLCELLULOSE SODIUM, UNSPECIFIED; XANTHAN GUM; TRIBASIC CALCIUM PHOSPHATE; SACCHARIN SODIUM; STEVIA REBAUDIANA WHOLE; SODIUM COCOYL GLUTAMATE; SODIUM LAURYL SULFATE; MENTHOL, UNSPECIFIED FORM; CHAMOMILE; CALENDULA OFFICINALIS FLOWER; ROSEMARY; SCUTELLARIA BAICALENSIS ROOT; GREEN TEA LEAF; FOENICULUM VULGARE WHOLE; WATER

83672-002_ETT HOJAKDO Sensitivity and Cavity Care

active ingredient

Potassium Nitrate 5%

Sodium Fluoride 0.315%

Keep out of reach of children under 6 years of age. If more than used for brushing is accidentally swallowed, get medical help or contact a Poison Control Center right away

Purpose

Antihypersensitivity, Anticavity

Uses

- Builds increasing protection against painful sensitivity of the
teeth to cold, heat, acids, sweets or contact
- Helps protect against cavities

Warnings

Ask a dentist before use if you have
• Bleeding or redness lasting more than 2 weeks
• Pain, swelling, pus, loose teeth, or more spacing between teeth
These may be signs of periodontitis, a serious form of gum disease

Directions

Supervise children as necessary until capable of using without supervision

Adults and children 12 years of age and older: Brush teeth thoroughly, preferably after each meal or at least 3 minutes twice a day (morning and evening), or as directed by a dentist or a physician

Children under 12 years of age: Consult a dentist or doctor

Inactive Ingredients

Glycerin, Water, Hydrated Silica, Hydroxyapatite, Sorbitol, Cellulose Gum, Sodium Fluoride, Xylitol, Sodium Saccharin, Xanthan Gum, Foeniculum Vulgare Oil, Menthol, Sodium Cocoyl Glutamate, Chamomilla Recutita Flower Extract, Calendula Officinalis Flower Extract, Rosmarinus Officinalis (Rosemary) Leaf Extract, Scutellaria Baicalensis Root Extract, Camellia Sinensis Leaf Extract, Stevia Rebaudiana Extract